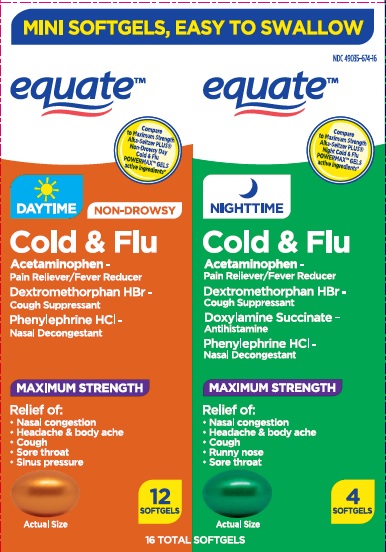 DRUG LABEL: Maximum Strength Non Drowsy Day and Night Cold and Flu
NDC: 49035-674 | Form: KIT | Route: ORAL
Manufacturer: WAL-MART STORES INC
Category: otc | Type: HUMAN OTC DRUG LABEL
Date: 20260126

ACTIVE INGREDIENTS: ACETAMINOPHEN 325 mg/1 1; DEXTROMETHORPHAN HYDROBROMIDE 10 mg/1 1; PHENYLEPHRINE HYDROCHLORIDE 5 mg/1 1; ACETAMINOPHEN 325 mg/1 1; DEXTROMETHORPHAN HYDROBROMIDE 10 mg/1 1; DOXYLAMINE SUCCINATE 6.25 mg/1 1; PHENYLEPHRINE HYDROCHLORIDE 5 mg/1 1
INACTIVE INGREDIENTS: GELATIN; GLYCERIN; POLYETHYLENE GLYCOL 400; SORBITAN; SORBITOL; TITANIUM DIOXIDE; FD&C YELLOW NO. 6; WATER; POVIDONE; POTASSIUM ALUMINUM DISILICATE; PROPYLENE GLYCOL; GELATIN; GLYCERIN; WATER; TITANIUM DIOXIDE; FD&C BLUE NO. 1; SORBITOL; PROPYLENE GLYCOL; POLYETHYLENE GLYCOL 400; POVIDONE; D&C YELLOW NO. 10; SORBITAN; POTASSIUM ALUMINUM DISILICATE

Equate Maximum Strength Non Drowsy Day and Night Cold & Flu

PATIENT INFORMATION

Do not take these products at the same time.

Drug Facts

Non Drowsy Day Cold & Flu

Active ingredients (in each capsule)

Acetaminophen 325 mg

Dextromethorphan hydrobromide 10 mg

Phenylephrine hydrochloride 5 mg

Purposes

Pain reliever/fever reducer

Cough suppressant

Nasal decongestant

Uses

· temporarily relieves these symptoms due to a cold or flu:

· minor aches and pains · headache · cough

· sore throat · nasal and sinus congestion

· temporarily reduces fever

Warnings

Liver warning: This product contains acetaminophen. Severe liver damage may occur if you take

· more than 4,000 mg of acetaminophen in 24 hours

· with other drugs containing acetaminophen

· 3 or more alcoholic drinks every day while using this product

Allergy alert: Acetaminophen may cause severe skin or severe

allergic reactions. Symptoms may include:

· skin reddening · blisters · rash · hives

· facial swelling · asthma (wheezing) · shock

If a skin or general allergic reaction occurs, stop use and seek medical help right away.

Sore throat warning: If sore throat is severe, persists for more than

2 days, is accompanied or followed by fever, headache, rash, nausea,

or vomiting, consult a doctor promptly.

Do not use

● with any other drug containing acetaminophen (prescription or

nonprescription). If you are not sure whether a drug contains

acetaminophen, ask a doctor or pharmacist.

● if you are now taking a prescription monoamine oxidase inhibitor

(MAOI) (certain drugs for depression, psychiatric, or emotional

conditions, or Parkinson's disease), or for 2 weeks after stopping

the MAOI drug. If you do not know if your prescription drug contains

an MAOI, ask a doctor or pharmacist before taking this product.

● if you have ever had an allergic reaction to this product or any of its

ingredients

● in children under 12 years of age

Ask a doctor before use if you have

● liver disease ● heart disease ● high blood pressure

● thyroid disease ● diabetes

● cough with excessive phlegm (mucus)

● difficulty in urination due to enlargement of the prostate gland

● persistent or chronic cough such as occurs with smoking, asthma,

or emphysema

Ask a doctor or pharmacist before use if you are taking the blood thinning drug warfa

When using this product do not exceed recommended dosage

Stop use and ask a doctor if

· pain, cough, or nasal congestion gets worse or lasts more than

7 days

· fever gets worse or lasts more than 3 days

· redness or swelling is present

· new symptoms occur

· cough comes back or occurs with rash or headache that lasts.

These could be signs of a serious condition.

· nervousness, dizziness, or sleeplessness occurs

PREGNANCY OR BREAST FEEDING

If pregnant or breast-feeding, ask a health professional before use.

Keep out of reach of children. In case of overdose, get medical help or contact a Poison Control Center right away. Quick medical attention is critical for adults as well as for children even if you do not notice any signs or symptoms.

Directions

· do not take more than the recommended dose

· adults and children 12 years and over: take 2 capsules with water

every 4 hours. Do not exceed 10 capsules in 24 hours or as

directed by a doctor.

· children under 12 years: do not use

Other information

● store at room temperature. Avoid temperatures above 25°C (77°F).

Inactive ingredients

FD&C yellow #6, gelatin,
glycerin, potassium aluminum silicate, polyethylene glycol, povidone,
propylene glycol, purified water, sorbitol , titanium
dioxide

Questions or comments? 1-888-333-9792

Maximum Strength Night Cold & Flu

Active ingredients (in each capsule)

Acetaminophen 325 mg

Dextromethorphan hydrobromide 10 mg

Doxylamine succinate 6.25 mg

Phenylephrine hydrochloride 5 mg

Purposes

Pain reliever/fever reducer

Cough suppressant

Antihistamine

Nasal decongestant

Uses

· temporarily relieves these symptoms due to a cold or flu:

· minor aches and pains · headache

· nasal and sinus congestion · cough · sore throat

· runny nose · sneezing

· temporarily reduces fever

Warnings

Liver warning: This product contains acetaminophen. Severe liver damage may occur if you take

· more than 4,000 mg of acetaminophen in 24 hours

· with other drugs containing acetaminophen

· 3 or more alcoholic drinks every day while using this product

Allergy alert: Acetaminophen may cause severe skin or severe

allergic reactions. Symptoms may include:

· skin reddening · blisters · rash · hives

· facial swelling · asthma (wheezing) · shock

If a skin or general allergic reaction occurs, stop use and seek medical help right away.

Sore throat warning: If sore throat is severe, persists for more than

2 days, is accompanied or followed by fever, headache, rash, nausea,

or vomiting, consult a doctor promptly.

Do not use to sedate children.

Do not use

● with any other drug containing acetaminophen (prescription or

nonprescription). If you are not sure whether a drug contains

acetaminophen, ask a doctor or pharmacist.

● if you are now taking a prescription monoamine oxidase inhibitor

(MAOI) (certain drugs for depression, psychiatric, or emotional

conditions, or Parkinson's disease), or for 2 weeks after stopping

the MAOI drug. If you do not know if your prescription drug contains

an MAOI, ask a doctor or pharmacist before taking this product.

● if you have ever had an allergic reaction to this product or any of its

ingredients

● in children under 12 years of age

Ask a doctor before use if you have

● liver disease ● heart disease ● high blood pressure

● thyroid disease ● diabetes ● glaucoma

● cough with excessive phlegm (mucus)

● a breathing problem such as emphysema or chronic bronchitis

● difficulty in urination due to enlargement of the prostate gland

● persistent or chronic cough such as occurs with smoking, asthma,

or emphysema

Ask a doctor or pharmacist before use if you are

● taking the blood thinning drug warfarin

● taking sedatives or tranquilizers

When using this product

● do not exceed recommended dosage

● may cause marked drowsiness

● avoid alcoholic drinks

● alcohol, sedatives, and tranquilizers may increase drowsiness

● be careful when driving a motor vehicle or operating machinery

● excitability may occur, especially in children

Stop use and ask a doctor if

· pain, cough, or nasal congestion gets worse or lasts more than

7 days

· fever gets worse or lasts more than 3 days

· redness or swelling is present

· new symptoms occur

· cough comes back or occurs with rash or headache that lasts.

These could be signs of a serious condition.

· nervousness, dizziness, or sleeplessness occurs

PREGNANCY OR BREAST FEEDING

If pregnant or breast-feeding, ask a health professional before use.

Keep out of reach of children. In case of overdose, get medical help

or contact a Poison Control Center right away. Quick medical attention is critical for adults as well as for children even if you do not notice any signs or symptoms.

Directions

· do not take more than the recommended dose

· adults and children 12 years and over: take 2 capsules with water

every 4 hours. Do not exceed 10 capsules in 24 hours or as

directed by a doctor.

· children under 12 years: do not use

Other information

● store at room temperature. Avoid temperatures above 25°C (77°F).

INACTIVE INGREDIENT

Inactive ingredients FD&C Blue #1, FD&C yellow
#10, gelatin, glycerin, potassium aluminum silicate, polyethylene glycol ,
povidone, propylene glycol, purified water, sorbitol
sorbitan solution, titanium dioxide

Questions or comments?1-888-287-1915

PRINCIPAL DISPLAY PANEL

EQUATE Maximum Strength Day & Night Cold & Flu

Compare to the active ingredients in
Alka-Seltzer PLUS® Maximum Strength Day
and Night Cold & Flu POWERMAX™ GELS

DAY NON DROWSY

Acetaminophen / Pain Reliever-Fever Reducer

Dextromethorphan HBr / Cough Suppressant

Phenylephrine HCl / Nasal Decongestant

Relieves:

Nasal Congestion
Headache & Body Ache
Cough
Sore Throat
Sinus Pressure

12 SOFTGELS

NIGHT TIME

Acetaminophen / Pain Reliever-Fever Reducer

Dextromethorphan HBr / Cough Suppressant

Doxylamine Succinate / Antihistamine

Phenylephrine HCl / Nasal Decongestant

Nasal Congestion
Headache & Body Ache
Cough
Runny Nose
Sore Throat
4 SOFTGELS

16 SOFTGELS TOTAL

*This product is not manufactured or distributed by Bayer
HealthCare LLC, owner of the registered trademark
Alka-Seltzer PLUS® POWERMAX™ GELS.